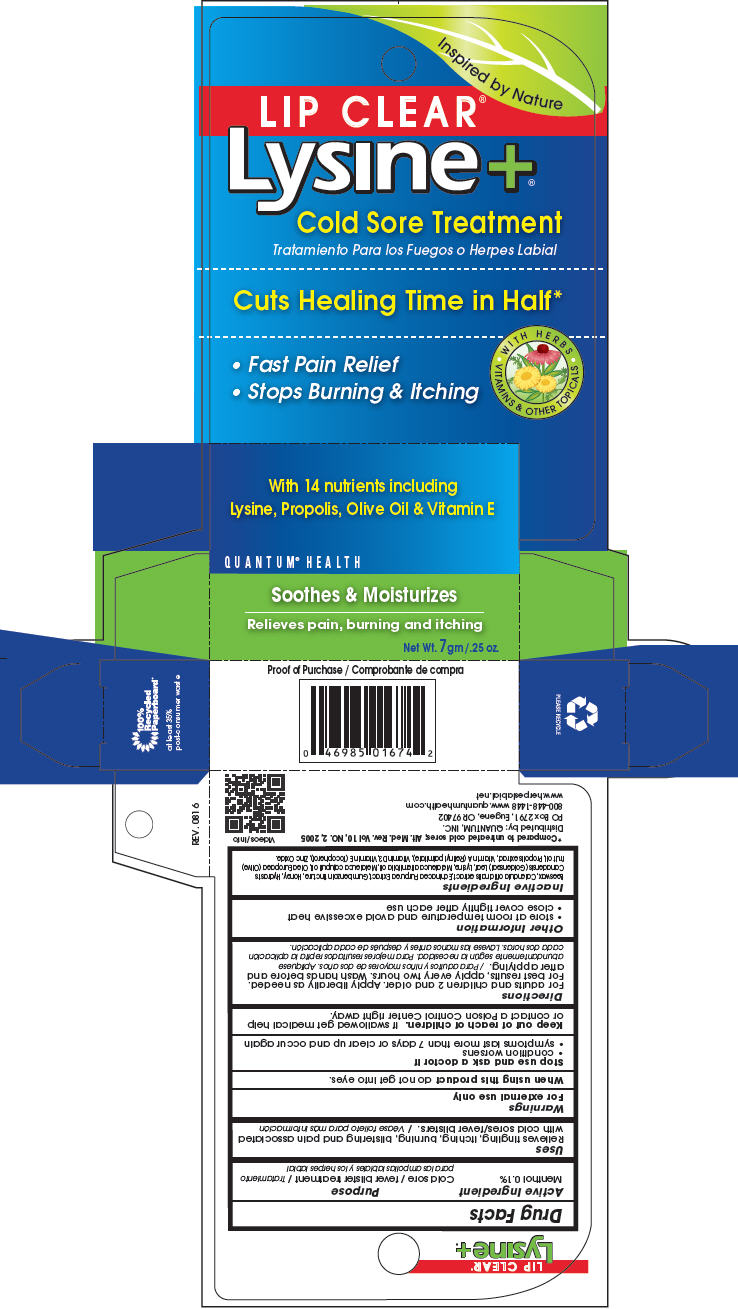 DRUG LABEL: Lip Clear Lysine Plus
NDC: 70084-320 | Form: OINTMENT
Manufacturer: Quantum, Inc.
Category: otc | Type: HUMAN OTC DRUG LABEL
Date: 20251020

ACTIVE INGREDIENTS: MENTHOL, UNSPECIFIED FORM 1 mg/1 g
INACTIVE INGREDIENTS: CALENDULA OFFICINALIS FLOWER; ECHINACEA PURPUREA WHOLE; BENZOIN RESIN; HONEY; GOLDENSEAL; LYSINE HYDROCHLORIDE; TEA TREE OIL; MELALEUCA CAJUPUTI LEAF OIL; OLIVE OIL; PROPOLIS WAX; VITAMIN A PALMITATE; CHOLECALCIFEROL; .ALPHA.-TOCOPHEROL; ZINC OXIDE; YELLOW WAX

Lip Clear®Lysine +®

Drug Facts

Active Ingredient

Menthol 0.1%

Purpose

Cold sore / fever blister treatment / Tratamiento para las ampollas labiales y los herpes labial

Uses

Relieves tingling, itching, burning, blistering and pain associated with cold sores/fever blisters. / Véase folleto para más información

Warnings

For external use only

When using this productdo not get into eyes.

Stop use and ask a doctor if

- condition worsens
- symptoms last more than 7 days or clear up and occur again

Keep out of reach of children.If swallowed get medical help or contact a Poison Control Center right away.

Directions

For adults and children 2 and older. Apply liberally as needed. For best results, apply every two hours. Wash hands before and after applying. / Para adultos y niños mayores de dos años. Aplíquese abundantemente según la necesidad. Para mejores resultados repita la aplicación cada dos horas. Lávese las manos antes y después de cada aplicación.

Other Information

- store at room temperature and avoid excessive heat
- close cover tightly after each use

Inactive Ingredients

Beeswax, Calendula officinalis extract, Echinacea Purpurea Extract, Gum benzoin tincture, Honey, Hydrastis Canadensis (Goldenseal) Leaf, Lysine, Melaleuca alternifolia oil, Melaleuca cajuputi oil, Olea Europaea (Olive) fruit oil, Propolis extract, Vitamin A (Retinyl palmitate), Vitamin D3, Vitamin E (Tocopherol), Zinc Oxide.

Distributed by: QUANTUM, INC.
PO Box 2791, Eugene, OR 97402

PRINCIPAL DISPLAY PANEL - 7 gm Tube Carton

Inspired by Nature

LIP CLEAR®
Lysine+®

Cold Sore Treatment

Cuts Healing Time in Half*

WITH HERBS
VITAMINS & OTHER TOPICALS

- Fast Pain Relief
- Stops Burning & Itching

With 14 nutrients including
Lysine, Propolis, Olive Oil & Vitamin E

QUANTUM®HEALTH

Soothes & Moisturizes

Relieves pain, burning and itching

Net Wt. 7gm /.25 oz.